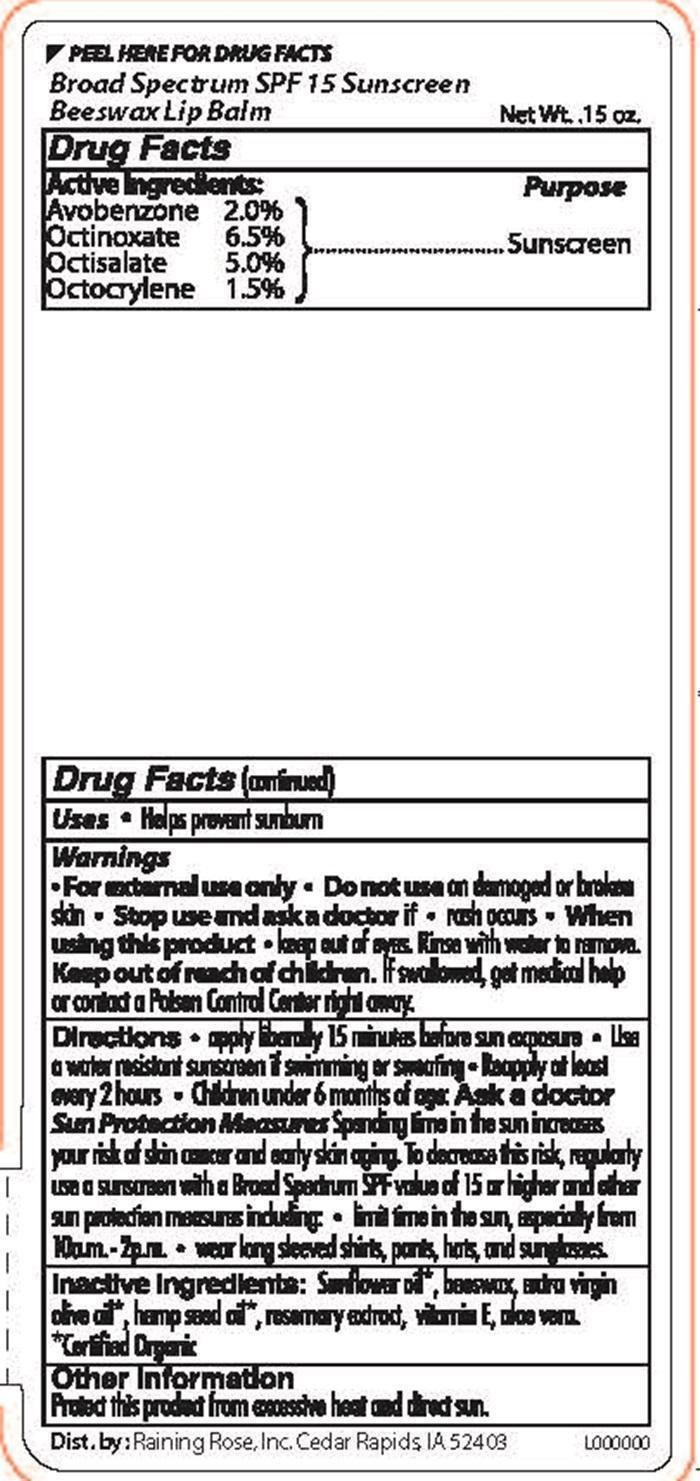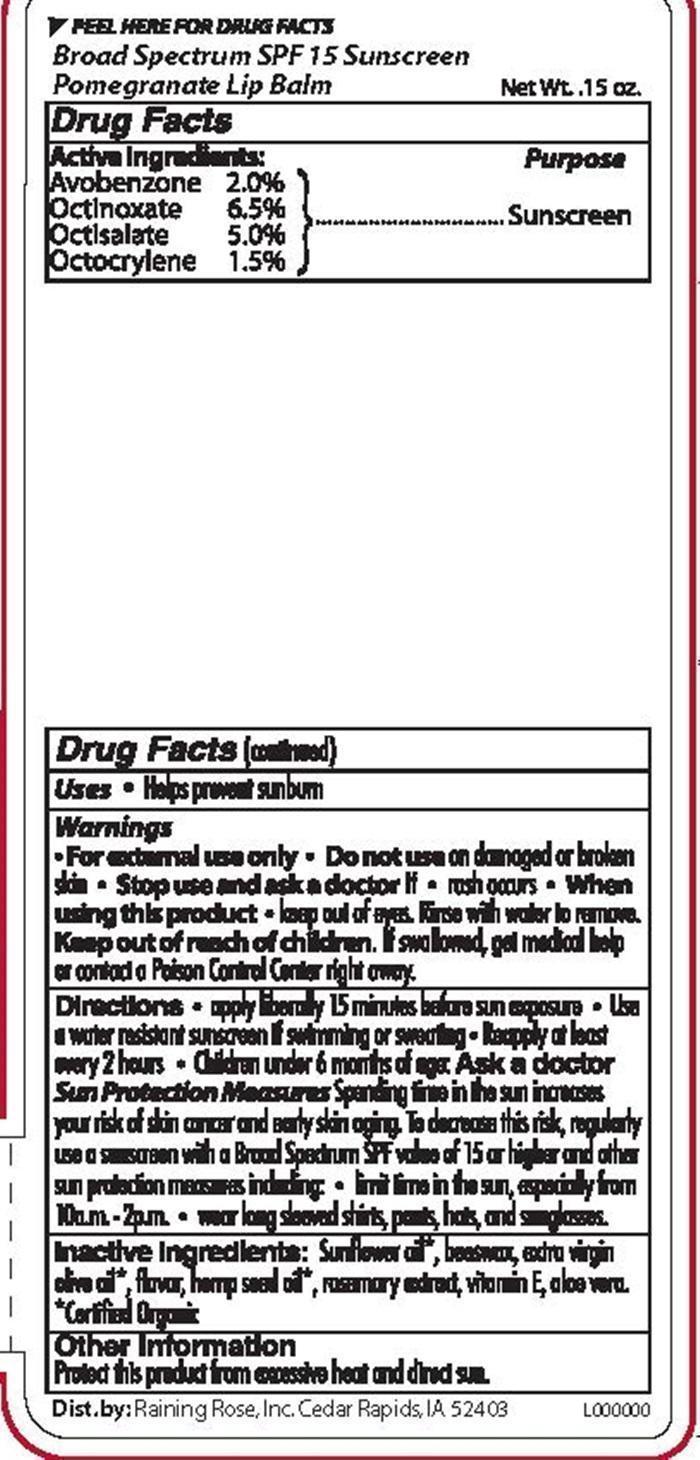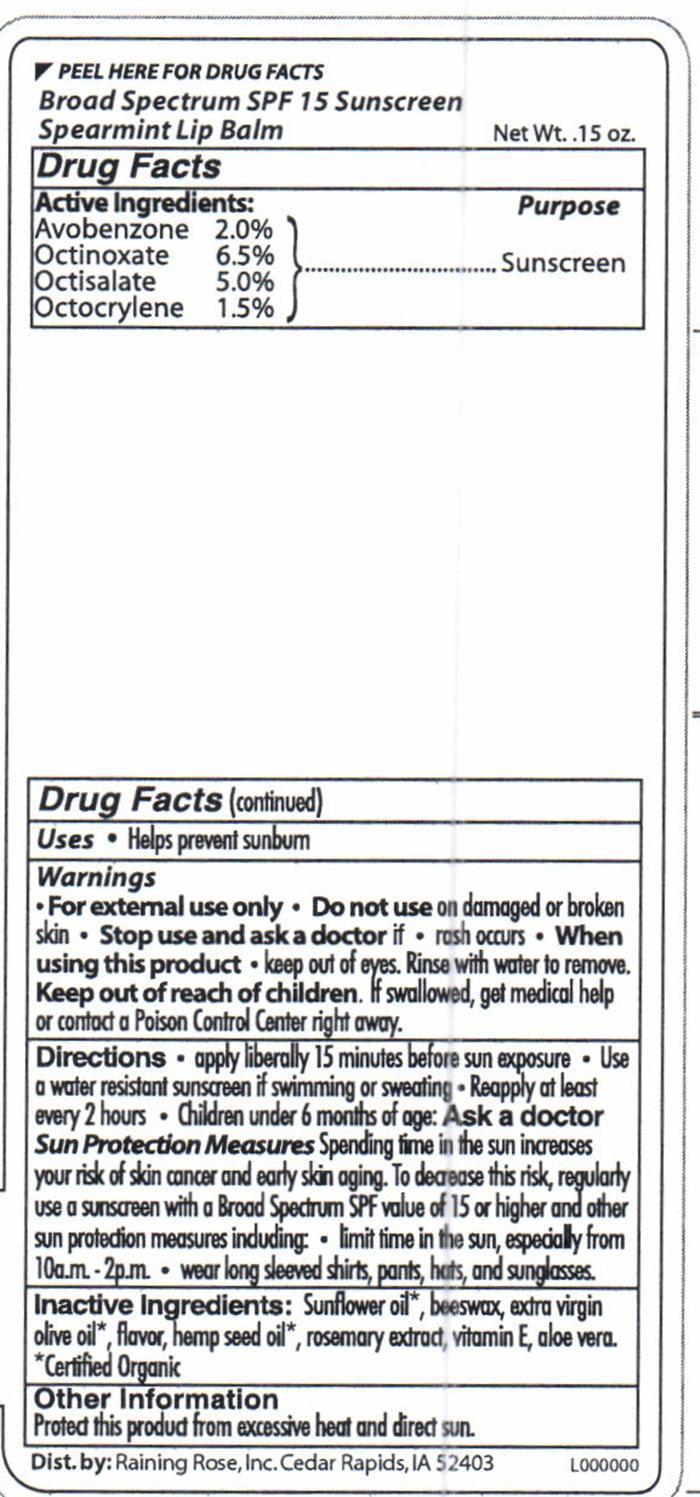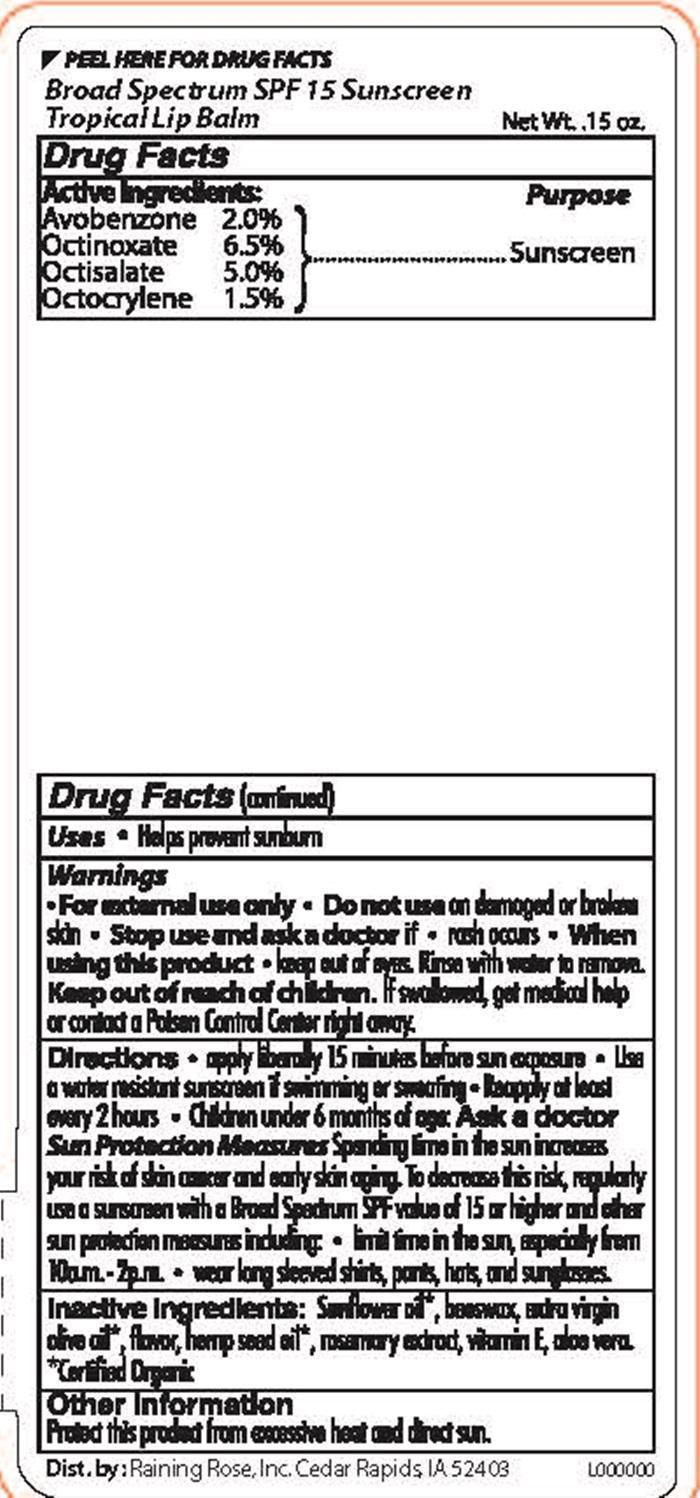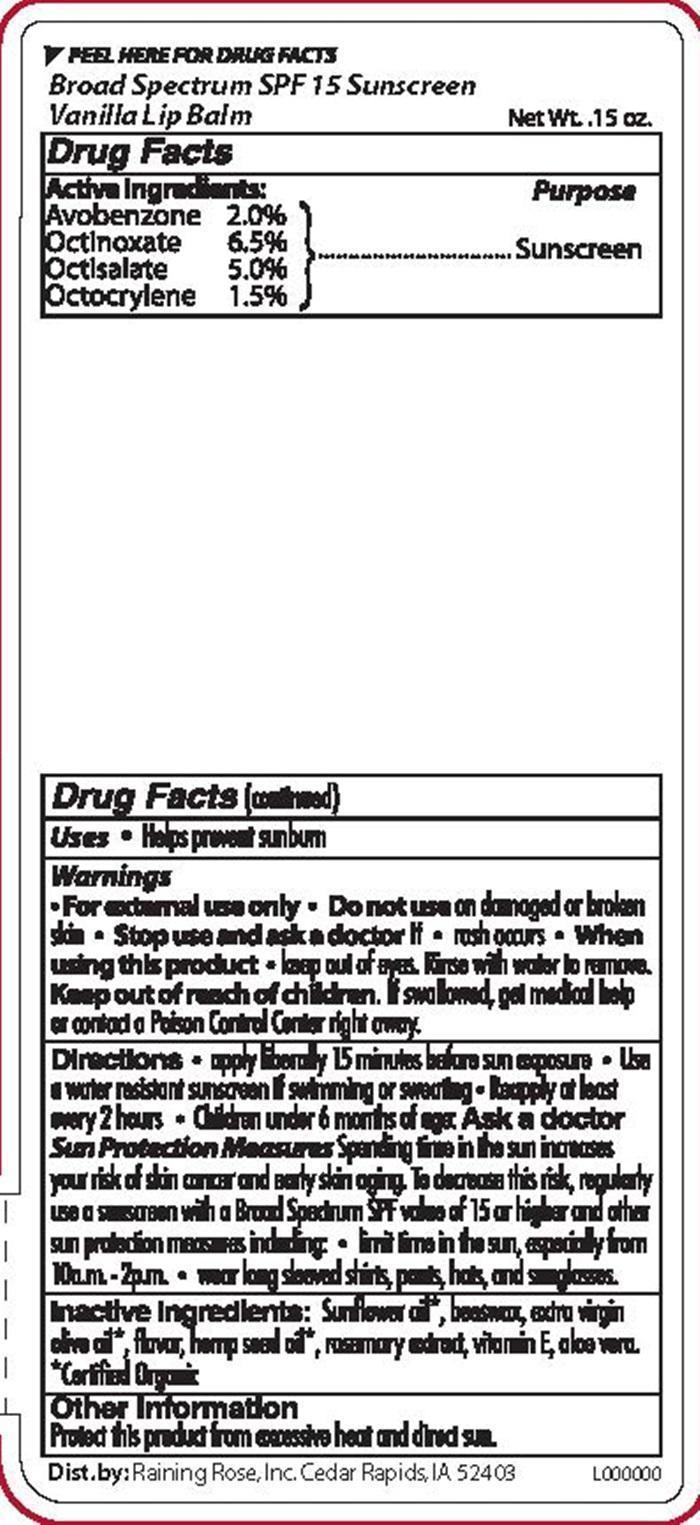 DRUG LABEL: Spearmint SPF 15 Lip

NDC: 65692-0301 | Form: STICK
Manufacturer: Raining Rose, Inc.
Category: otc | Type: HUMAN OTC DRUG LABEL
Date: 20171227

ACTIVE INGREDIENTS: AVOBENZONE 0.09 g/4.25 g; OCTINOXATE 0.28 g/4.25 g; OCTISALATE 0.21 g/4.25 g; OCTOCRYLENE 0.06 g/4.25 g
INACTIVE INGREDIENTS: SUNFLOWER OIL; YELLOW WAX; OLIVE OIL; SPEARMINT; CANNABIS SATIVA SEED OIL; ROSEMARY; .ALPHA.-TOCOPHEROL; ALOE VERA LEAF

PEEL HERE FOR DRUG FACTS Broad Spectrum SPF 15 Sunscreen Spearmint Lip Balm, Beeswax Lip Balm, Pomegranate Lip Balm, Tropical Lip Balm, Vanilla Lip Balm Drug Facts

Active Ingredients:
Avobenzone 2.0%
Octinoxate 6.5%
Octsalate 5.0%
Octocrylene 1.5%

Purpose

Sunscreen

Keep out of reach of children.

If swallowed, get medical help or contact a Poison Control Center right away.

Uses

Helps prevent sunburn

Warnings

For external use only

Do not use

on damaged or broken skin

Stop use and ask a doctor

if rash occurs

When using this product

keep out of eyes. Rinse well with water to remove.

Directions

apply liberally 15 minutes before sun exposure Use a water resistant sunscreen if swimming or sweating Reapply at least every 2 hours Children under 6 months of age: Ask a doctor
Sun Protection Measures Spending time in the sun increases your risk of skin cancer and early skin aging. To decrease this risk, regularly use a sunscreen with a broad Spectrum SPF value of 15 or higher and other sun protection measures including limit time in the sun, especially from 10a.m. - 2p.m. wear long sleeved shirts, pants, hats, and sunglasses.

Inactive Ingredients

Sunflower oil*, beeswax, extra virgin olive oil*, hemp seed oil*, rosemary extract, vitamin E, aloe vera
*Certified Organic

Other Information

Protect this product from excessive heat and direct sun.

Product Label Spearmint Lip Balm Beeswax Lip Balm Pomegranate Lip Balm Tropical Lip Balm Vanilla Lip Balm

Dist. by: Raining Rose, Inc. Cedar Rapids IA 52403 L000000
PEEL HERE FOR DRUG FACTS
Broad Spectrum SPF Sunscreen
NetWt. .15 oz

Spearmint Lip Balm
Beeswax Lip Balm
Pomegranate Lip Balm
Tropical Lip Balm
Vanilla Lip Balm